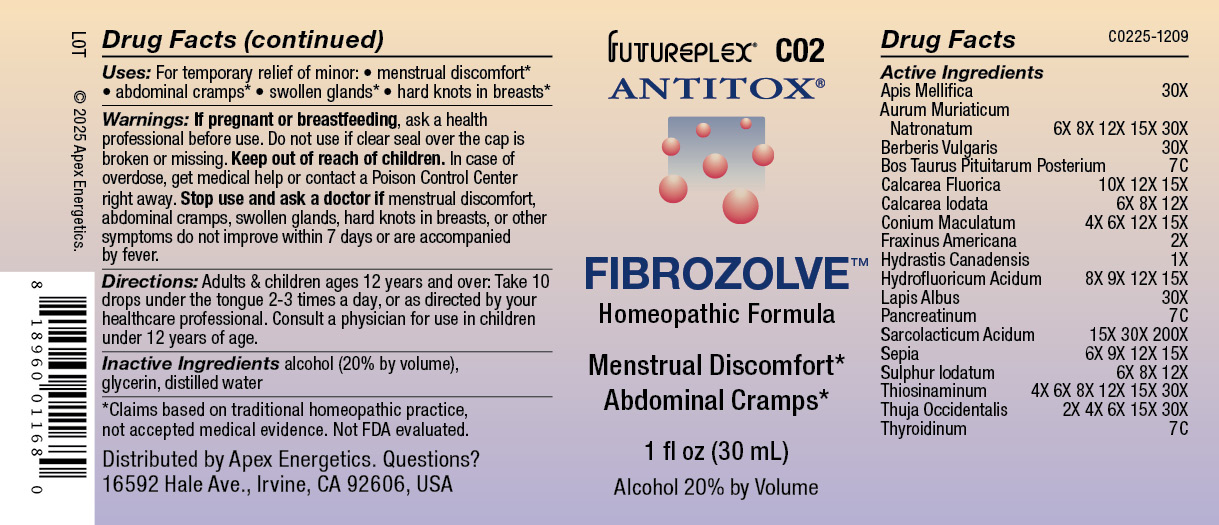 DRUG LABEL: C02
NDC: 63479-0302 | Form: SOLUTION/ DROPS
Manufacturer: Apex Energetics Inc.
Category: homeopathic | Type: HUMAN OTC DRUG LABEL
Date: 20251231

ACTIVE INGREDIENTS: CALCIUM HEXAFLUOROSILICATE 30 [hp_X]/1 mL; FRAXINUS AMERICANA BARK 2 [hp_X]/1 mL; LACTIC ACID, L- 200 [hp_X]/1 mL; ALLYLTHIOUREA 30 [hp_X]/1 mL; THUJA OCCIDENTALIS LEAFY TWIG 30 [hp_X]/1 mL; GOLDENSEAL 1 [hp_X]/1 mL; HYDROFLUORIC ACID 15 [hp_X]/1 mL; PANCRELIPASE 7 [hp_C]/1 mL; SODIUM TETRACHLOROAURATE 30 [hp_X]/1 mL; THYROID, UNSPECIFIED 7 [hp_C]/1 mL; CALCIUM FLUORIDE 15 [hp_X]/1 mL; SEPIA OFFICINALIS JUICE 15 [hp_X]/1 mL; SULFUR IODIDE 12 [hp_X]/1 mL; BOS TAURUS PITUITARY GLAND, POSTERIOR 7 [hp_C]/1 mL; CALCIUM IODIDE 12 [hp_X]/1 mL; BERBERIS VULGARIS ROOT BARK 30 [hp_X]/1 mL; CONIUM MACULATUM FLOWERING TOP 15 [hp_X]/1 mL; APIS MELLIFERA 30 [hp_X]/1 mL
INACTIVE INGREDIENTS: WATER; ALCOHOL; GLYCERIN

C02

Active Ingredients
Apis Mellifica | 30X
Aurum Muriaticum Natronatum | 6X 8X 12X 15X 30X
Berberis Vulgaris | 30X
Bos Taurus Pituitarum Posterium | 7C
Calcarea Fluorica | 10X 12X 15X
Calcarea Iodata | 4X 6X 8X 12X
Conium Maculatum | 4X 6X 12X 15X
Fraxinus Americana | 2X
Hydrastis Canadensis | 1X
Hydrofluoricum Acidum | 8X 9X 12X 15X
Lapis Albus | 30X
Pancreatinum | 7C
Sarcolacticum Acidum | 15X 30X 200X
Sepia | 6X 9X 12X 15X
Sulphur Iodatum | 6X 8X 12X
Thiosinaminum | 4X 6X 8X 12X 15X 30X
Thuja Occidentalis | 2X 4X 6X 15X 30X
Thyroidinum | 7C

INDICATIONS AND USAGE

Uses:

For temporary relief of minor:

menstrual discomfort*

abdominal cramps*

swollen glands*

hard knots in breasts*

*Claims based on traditional homeopathic practice, not accepted medical evidence. Not FDA evaluated.

Warnings:

PREGNANCY OR BREAST FEEDING

If pregnant or breastfeeding, ask a health professional before use.

Do not use if clear seal over the cap is broken or missing.

Keep out of reach of children. In case of overdose, get medical help or contact a Poison Control Center right away.

Stop use and ask a doctor if menstrual discomfort, abdominal cramps, swollen glands, hard knots in breasts, or other symptoms do not improve within 7 days or are accompanied by fever.

Directions:

Adults & children ages 12 years and over: Take 10 drops under the tongue 2-3 times a day, or as directed by your healthcare professional. Consult a physician for use in children under 12 years of age.

Inactive Ingredients

alcohol (20% by volume), glycerin, distilled water

Distributed by Apex Energetics. Questions?

16592 Hale Ave., Irvine, CA 92606, USA

PACKAGE LABEL

FUTUREPLEX® C02

ANTITOX®

FIBROZOLVE™

Homeopathic Formula

Menstrual Discomfort*

Abdominal Cramps*

1 fl oz (30 mL)

Alcohol 20% by Volume